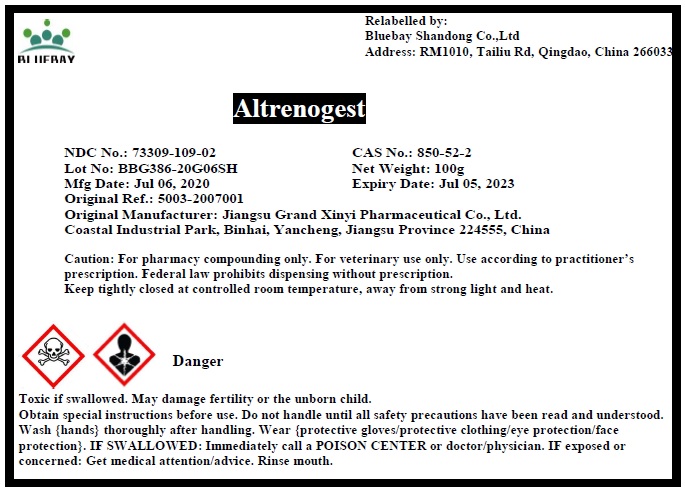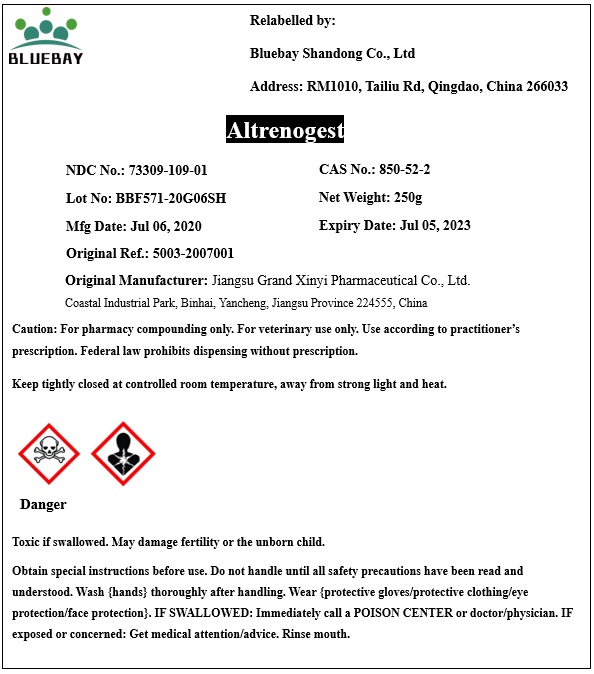 DRUG LABEL: Altrenogest
NDC: 73309-109 | Form: POWDER
Manufacturer: BLUEBAY SHANDONG CO.,LTD
Category: other | Type: BULK INGREDIENT
Date: 20210716

ACTIVE INGREDIENTS: ALTRENOGEST 1 g/1 g

Altrenogest